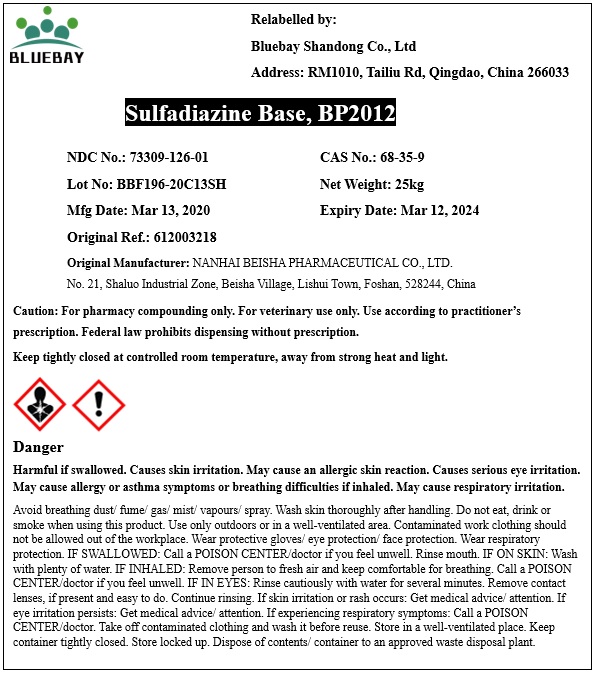 DRUG LABEL: Sulfadiazine Base
NDC: 73309-126 | Form: POWDER
Manufacturer: BLUEBAY SHANDONG CO.,LTD
Category: other | Type: BULK INGREDIENT
Date: 20200421

ACTIVE INGREDIENTS: SULFADIAZINE 1 kg/1 kg

Sulfadiazine Base